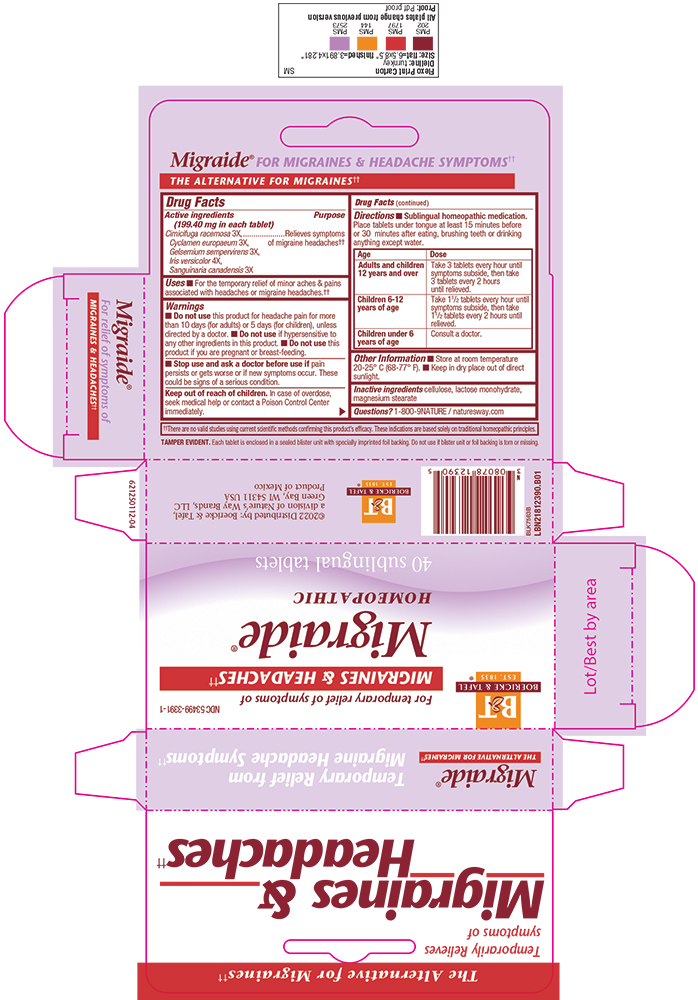 DRUG LABEL: Migraide
NDC: 53499-3391 | Form: tablet
Manufacturer: Schwabe North America, Inc.
Category: homeopathic | Type: HUMAN OTC DRUG LABEL
Date: 20220324

ACTIVE INGREDIENTS: CYCLAMEN PURPURASCENS TUBER 3 [hp_X]/1 1; BLACK COHOSH 3 [hp_X]/1 1; IRIS VERSICOLOR WHOLE 4 [hp_X]/1 1; GELSEMIUM SEMPERVIRENS WHOLE 3 [hp_X]/1 1; SANGUINARIA CANADENSIS ROOT 3 [hp_X]/1 1
INACTIVE INGREDIENTS: LACTOSE MONOHYDRATE; MAGNESIUM STEARATE; MICROCRYSTALLINE CELLULOSE

Migraide Tablets

Active Ingredient

Cimicifuga racemosa 3X

Cyclamen europaeum 3X

Gelsemium sempervirens 3X
Iris versicolor 4X
Sanguinaria canadensis 3X

Inactive Ingredient

Cellulose

Lactose Monohydrate

Magnesium Stearate

Dosage & Administration

Directions: Sublingual homeopathic medication.
Place tablets under tongue at least 15 minutes before or 30 minutes after eating, brushing teeth, or drinking anything except water.

Adults and Children 12 years and older: Take 3 tablets every hour until symptoms subside, then take 3 tablets every 2 hours until relieved.
Children 6-12 years of age: Take 1 1/2 tablets every hour until symptoms subside, then take 1 1/2 tablets every 2 hours until relieved.
Children under 6 years of age: Consult a doctor.

Purpose

For the temporary relief of minor aches and pains associated with headaches or migraine headaches.

Indications & Usage

For the temporary relief of minor aches and pains associated with headaches or migraine headaches.

Warings

Do not take this product for headache pain for more than 10 days (for adults) or 5 days (for children) unless directed by a doctor.

Do not use if hypersensitive to any other ingredients in this product.

Do not use this product if you are pregnant or breast-feeding.

Stop Use

Stop use and ask a doctor if pain persists or gets worse or if new symptoms occur.
These could be signs of a serious condition.

Pregnancy or Breast Feeding

Do not use this product if you are pregnant or breast-feeding.

Keep out of reach of children.

Overdose

In case of overdose, seek medical help or contact a Poison Control Center immediately.